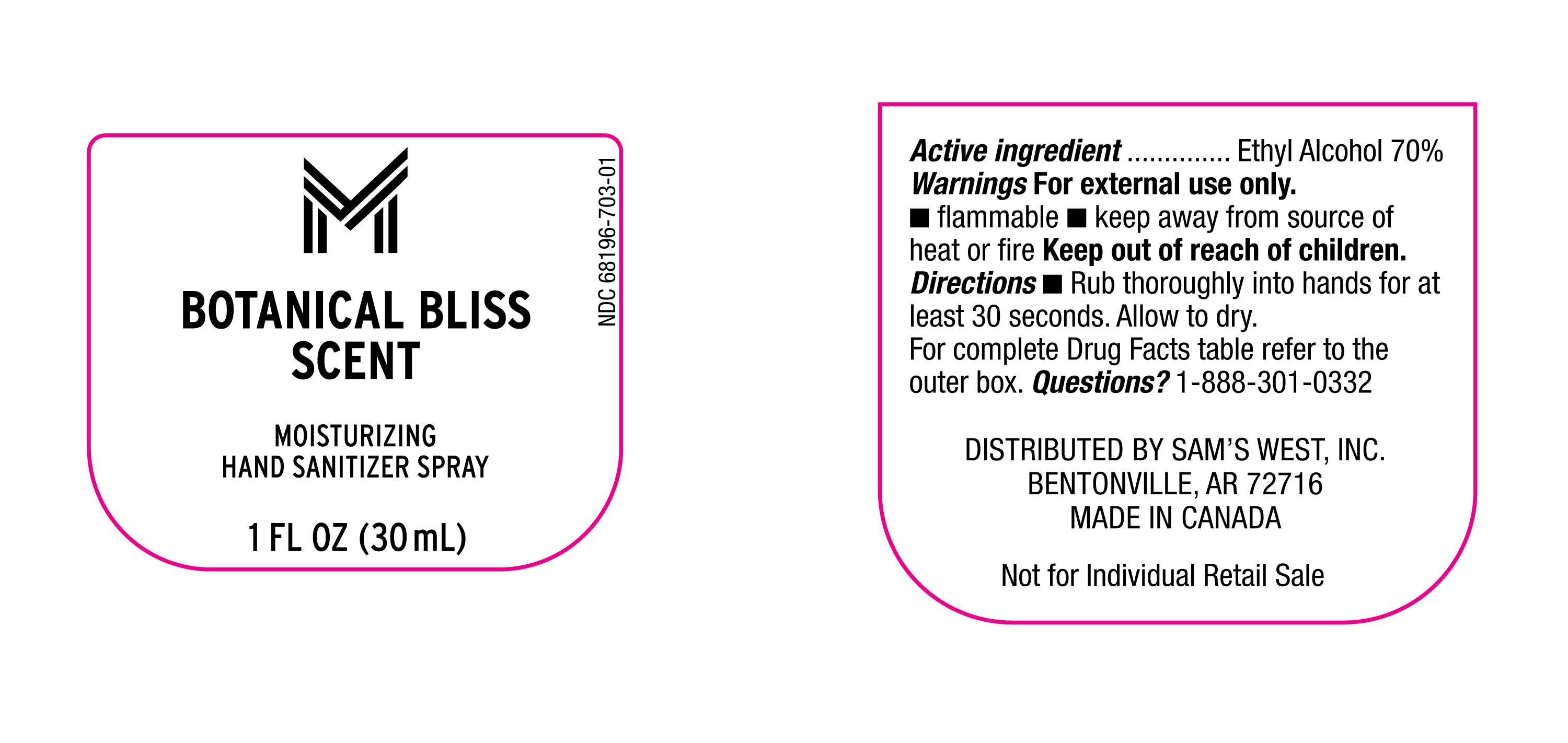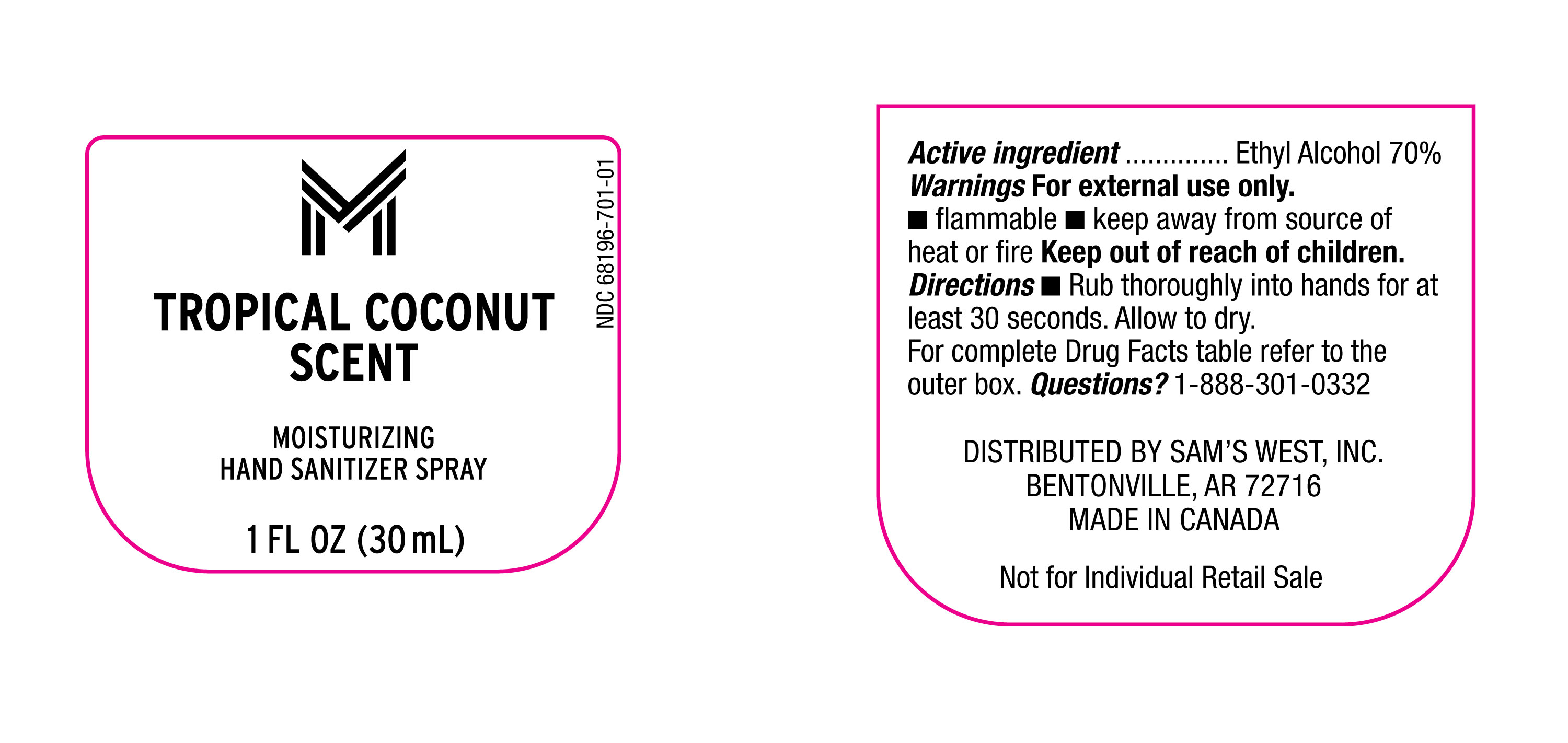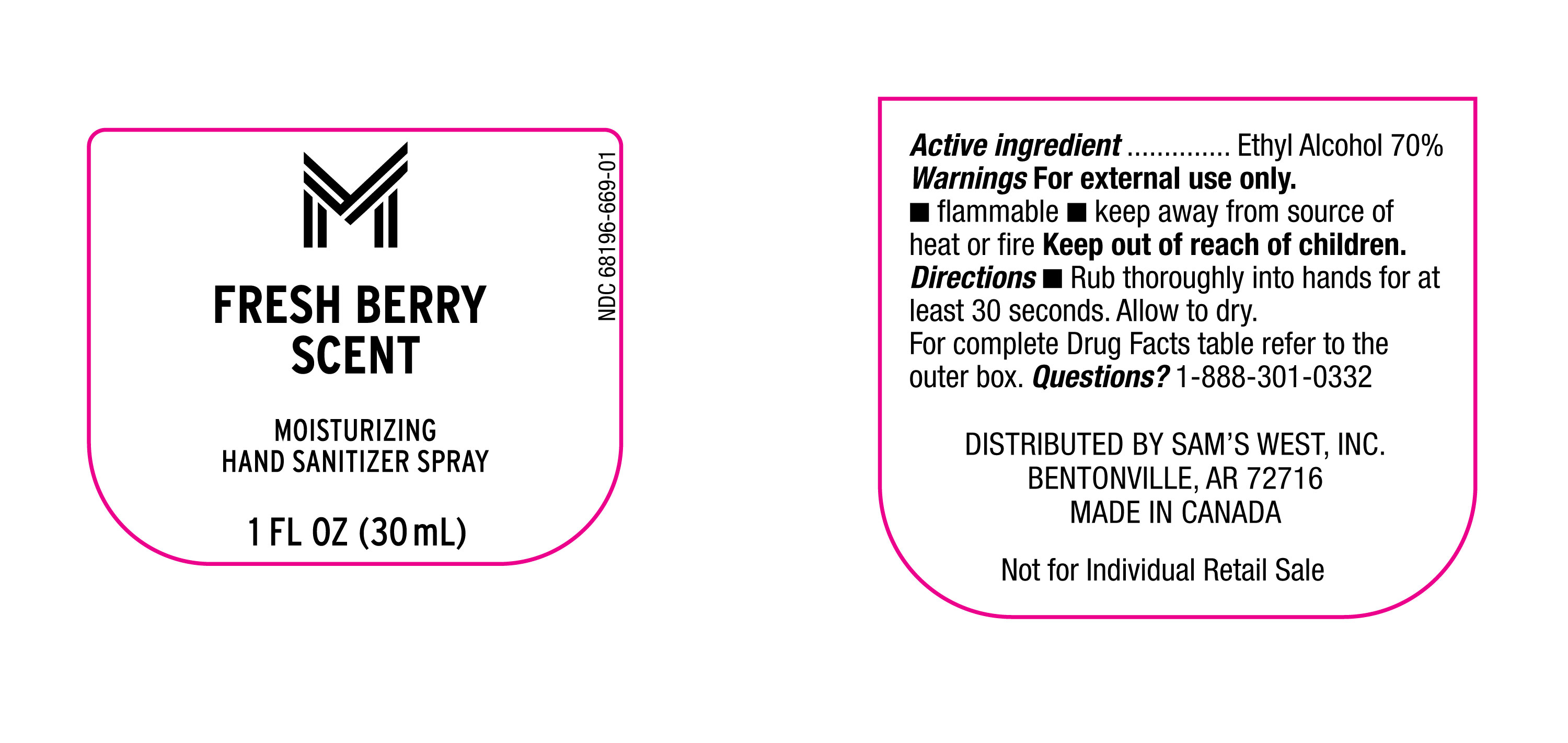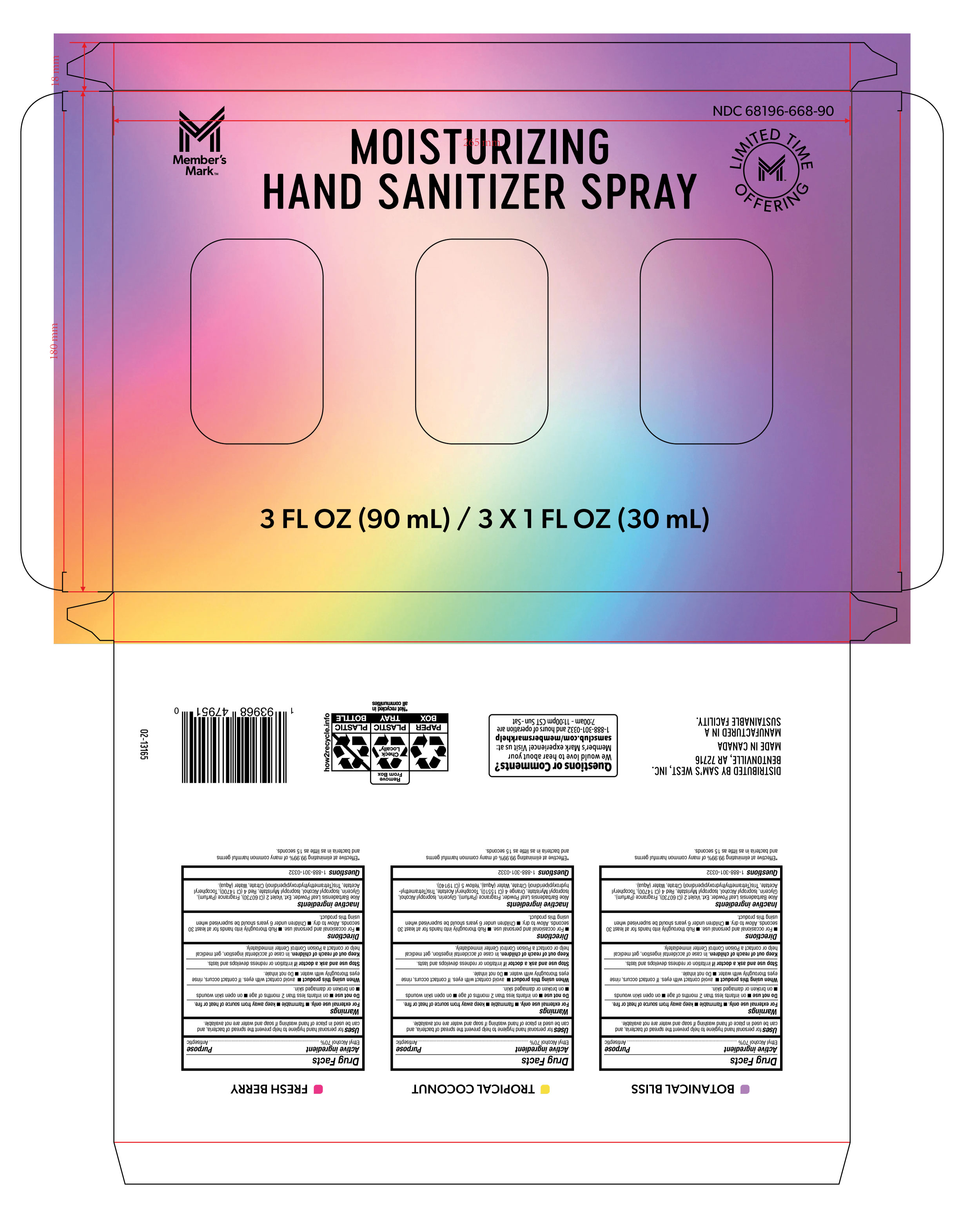 DRUG LABEL: Hand Sanitizer Kit
NDC: 68196-668 | Form: KIT | Route: TOPICAL
Manufacturer: SAM'S WEST INC
Category: otc | Type: HUMAN OTC DRUG LABEL
Date: 20250329

ACTIVE INGREDIENTS: ALCOHOL 70 mL/100 mL; ALCOHOL 70 mL/100 mL; ALCOHOL 70 mL/100 mL
INACTIVE INGREDIENTS: FRAGRANCE CLEAN ORC0600327; GLYCERIN; ISOPROPYL MYRISTATE; ALOE VERA LEAF; WATER; VIOLET 2; ISOPROPYL ALCOHOL; RED 4; ALPHA-TOCOPHEROL ACETATE; TRIS(TETRAMETHYLHYDROXYPIPERIDINOL) CITRATE; ISOPROPYL MYRISTATE; ALOE VERA LEAF; .ALPHA.-TOCOPHEROL ACETATE; TRIS(TETRAMETHYLHYDROXYPIPERIDINOL) CITRATE; WATER; RED 4; GLYCERIN; ISOPROPYL ALCOHOL; FRAGRANCE CLEAN ORC0600327; VIOLET 2; ALOE VERA LEAF; ISOPROPYL MYRISTATE; WATER; TRIS(TETRAMETHYLHYDROXYPIPERIDINOL) CITRATE; ORANGE 4; ALPHA-TOCOPHEROL ACETATE; ISOPROPYL ALCOHOL; GLYCERIN; YELLOW 5; FRAGRANCE CLEAN ORC0600327

NDC-68196-669, 68196-701, 68196-703, Outer box 68196-668-90

Active Ingredient

Ethyl Alcohol 70%

Purpose

Antiseptic

Uses

For Personal hand hygine to help prevent the spread of bacteria, and can be used in place of hand washing if soap and wter are not available.

Warnings

For eternal use only.

- Flammable
- Keep away from source of heat or fire.

Do not use

- On inants less than 2 months of age
- on open skin wounds.
- on broken or damaged skin.

When using this product

- Avoid contact with eyes. If contact occurs, rinse eyes thoroughly with water.
- Do not inhale.

Stop use and ask a doctor

if irritation or redness develops and lasts.

Keep out of reach of children.

In case of accidental ingestion, get medical help or contact a Poison Control Center immediately.

Directions

- For Occassional and personal use.
- Rub thoroughly into hands for at least 30 seconds. Allow to dry.
- Children under 6 years should be supervised when using this product.

Questions

1-888-301-0332

Inactive Ingredients (Botanical Bliss)

Aloe Barbadensis Leaf Powder, Ext. Violet 2 (CI 60730), Fragrance (Parfum), Glycerin, Isopropyl Alcohol, Isopropyl Myristate, Red 4 (CI 14700), Tocopheryl Acetate, Tris(Tetramethylhydroxypiperidinol) Citrate, Water (Aqua).

Inactive Ingredients (Tropical Coconut)

Aloe Barbadensis Leaf Powder, Fragrance (Parfum), Glycerin, Isopropyl Alcohol, Isopropul Myristate, Orange 4 (CI 15510), Tocopheryl Acetate, Tris (Tetramethylhydroxypiperidinol) Citrate, Water (Aqua), Yellow 5 (CI 19140)

Inactive Ingredients (Fresh Berry)

Aloe Barbadensis Leaf Powder, Ext. Violet 2 (CI 60730), Fragrance (Parfum), Glycerin, Isopropyl Alcohol, Isopropyl Myristate, Red 4 (CI 14700), Tocopheryl Acetate, Tris(Tetramethylhydroxypiperidinol) Citrate, Water (Aqua).